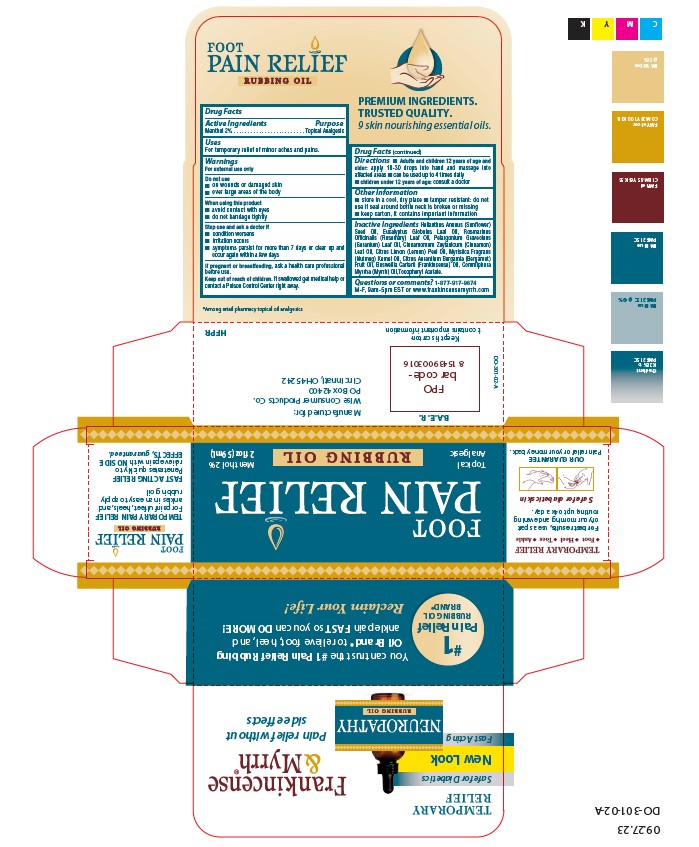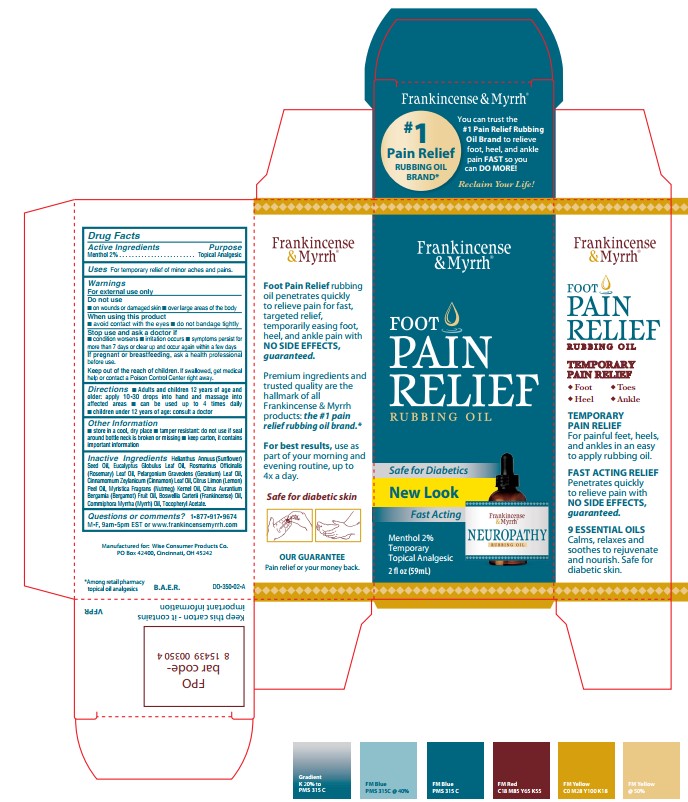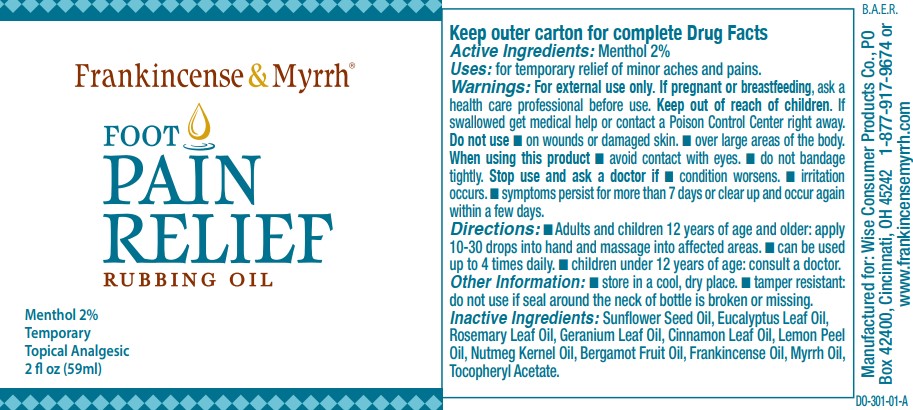 DRUG LABEL: Frankincense and Myrrh Foot Pain Relief
NDC: 42346-302 | Form: OIL
Manufacturer: WISE CONSUMER PRODUCTS CO.
Category: otc | Type: HUMAN OTC DRUG LABEL
Date: 20251226

ACTIVE INGREDIENTS: MENTHOL 20 mg/1 mL
INACTIVE INGREDIENTS: SUNFLOWER OIL; EUCALYPTUS OIL; LEMON OIL; ROSEMARY OIL; NUTMEG OIL; BERGAMOT OIL; CINNAMON LEAF OIL; FRANKINCENSE OIL; GERANIUM OIL, ALGERIAN TYPE; MYRRH OIL; ALPHA-TOCOPHEROL ACETATE

Active Ingredients

Menthol 2%

Purpose

Menthol 2% . . . . . . . . . . . . . . . . . Topical Analgesic

Uses

For temporary relief of minor aches and pains.

Warnings

For external use only

Do not use
 on wounds or damaged skin
 over large areas of the body

When using this product
 avoid contact with eyes
 do not bandage tightly

Stop use and ask a doctor if
 condition worsens
 irritation occurs
 symptoms persist for more than 7 days or clear up and occur again within a few days

PREGNANCY OR BREAST FEEDING

If pregnant or breastfeeding, ask a health care professional before use.

Keep out of reach of children. If swallowed get medical help or contact a Poison Control Center right away.

Directions

 Adults and children 12 years of age and older: apply 10-30 drops into hand and massage into affected areas
 can be used up to 4 times daily
 children under 12 years of age: consult a doctor

Other Information

 store in a cool, dry place

 tamper resistant: do not use if seal around bottle neck is broken or missing

 keep carton, it contains important information

Inactive Ingredients

Helianthus Annuus (Sunflower) Seed Oil, Eucalyptus Globulus Leaf Oil, Rosmarinus Officinalis (Rosemary) Leaf Oil, Pelargonium Graveolens (Geranium) Leaf Oil, Cinnamomum Zeylanicum (Cinnamon) Leaf Oil, Citrus Limon (Lemon) Peel Oil, Myristica Fragrans (Nutmeg) Kernel Oil, Citrus Aurantium Bergamia (Bergamot) Fruit Oil, Boswellia Carterii (Frankincense) Oil, Commiphora Myrrha (Myrrh) Oil,Tocopheryl Acetate.

Questions or comments?

1-877-917-9674
M-F, 9am-5pm EST or www.frankincensemyrrh.com

PACKAGE LABEL

Frankincense & Myrrh

Foot

Pain Relief

Topical Analgesic

Rubbing Oil

Menthol 2%

2 fl oz (59mL)